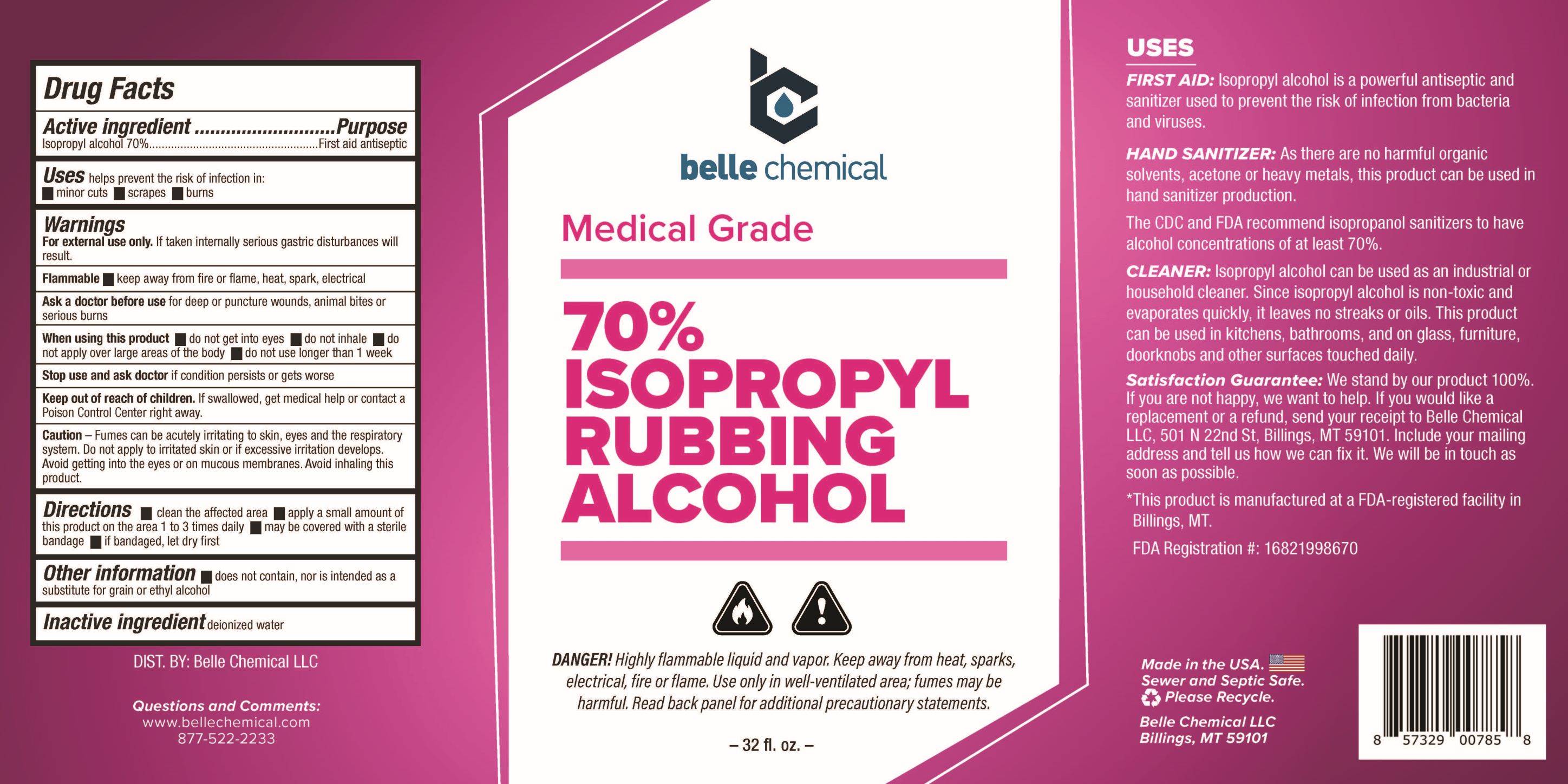 DRUG LABEL: 70% Isopropyl Rubbing Alcohol
NDC: 82771-070 | Form: SOLUTION
Manufacturer: Belle Chemical LLC
Category: otc | Type: HUMAN OTC DRUG LABEL
Date: 20250425

ACTIVE INGREDIENTS: ISOPROPYL ALCOHOL 1 mL/700 mg
INACTIVE INGREDIENTS: WATER

ACTIVE INGREDIENT

Isopropyl Alcohol 70%

Ask a doctor before usefor deep or puncture wounds, animal bites or serious burns

Keep out of reach of children. If swallowed, get medical help or contact a Poison Control Center right away.

PURPOSE

helps prevent the risk of infection in: minor cuts, scrapes, and burns

When using this product do not get into eyes, do not inhale, do not apply over large areas of the body, do not use longer than 1 week

Stop use and ask doctor if condition persists or gets worse

QUESTIONS

Questions and Comments: www.bellechemical.com; 877-522-2233

DOSAGE AND ADMINISTRATION

- clean the affected area
- apply a small amount of this product on the area 1 to 3 times daily
- may be covered with a sterile bandage
- if bandaged, let dry first

WARNINGS

For external use only. If taken internally serious gastric disturbances will result.

Flammable, keep away from fire or flame, heat, spark, electrical.

INACTIVE INGREDIENT

Water

INDICATIONS AND USAGE

helps prevent the risk of infection in:

- minor cuts
- scrapes
- burns